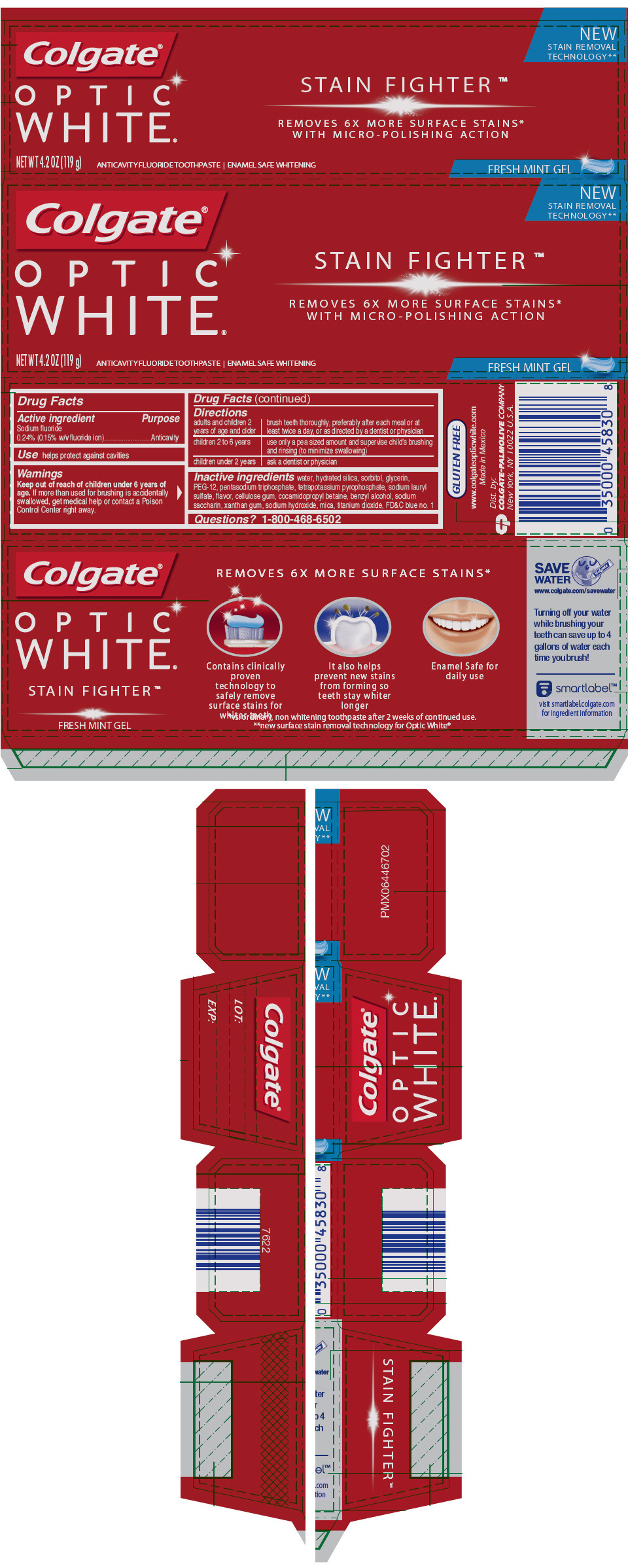 DRUG LABEL: Colgate Optic White Stain Fighter Fresh Mint
NDC: 35000-936 | Form: PASTE, DENTIFRICE
Manufacturer: COLGATE PALMOLIVE COMPANY
Category: otc | Type: HUMAN OTC DRUG LABEL
Date: 20191209

ACTIVE INGREDIENTS: SODIUM FLUORIDE 1 mg/1 g
INACTIVE INGREDIENTS: WATER 191.17 mg/1 g; HYDRATED SILICA; SORBITOL; GLYCERIN; POLYETHYLENE GLYCOL 600; SODIUM TRIPOLYPHOSPHATE ANHYDROUS; SODIUM PYROPHOSPHATE; SODIUM LAURYL SULFATE; CARBOXYMETHYLCELLULOSE SODIUM, UNSPECIFIED; COCAMIDOPROPYL BETAINE; BENZYL ALCOHOL; SACCHARIN SODIUM; XANTHAN GUM; SODIUM HYDROXIDE; MICA; TITANIUM DIOXIDE; FD&C BLUE NO. 1

Colgate® Optic White® Stain Fighter ™ Fresh Mint

Drug Facts

Active ingredient

Sodium fluoride 0.24% (0.15% w/v fluoride ion)

Purpose

Anticavity

Use

helps protect against cavities

Warnings

Keep out of reach of children under 6 years of age. If more than used for brushing is accidentally swallowed, get medical help or contact a Poison Control Center right away.

Directions

adults and children 2 years of age and older | brush teeth thoroughly, preferably after each meal or at least twice a day, or as directed by a dentist or physician
children 2 to 6 years | use only a pea sized amount and supervise child's brushing and rinsing (to minimize swallowing)
children under 2 years | ask a dentist or physician

Inactive ingredients

water, hydrated silica, sorbitol, glycerin, PEG-12, pentasodium triphosphate, tetrapotassium pyrophosphate, sodium lauryl sulfate, flavor, cellulose gum, cocamidopropyl betaine, benzyl alcohol, sodium saccharin, xanthan gum, sodium hydroxide, mica, titanium dioxide, FD&C blue no. 1

Questions?

1-800-468-6502

Dist. by:
COLGATE-PALMOLIVE COMPANY
New York, NY 10022 U.S.A.

PRINCIPAL DISPLAY PANEL - 119 g Tube Carton

NEW
STAIN REMOVAL
TECHNOLOGY**

Colgate®

OPTIC
WHITE®

STAIN FIGHTER ™

REMOVES 6X MORE SURFACE STAINS*
WITH MICRO-POLISHING ACTION

NET WT 4.2 OZ (119 g)
ANTICAVITY FLUORIDE TOOTHPASTE | ENAMEL SAFE WHITENING

FRESH MINT GEL